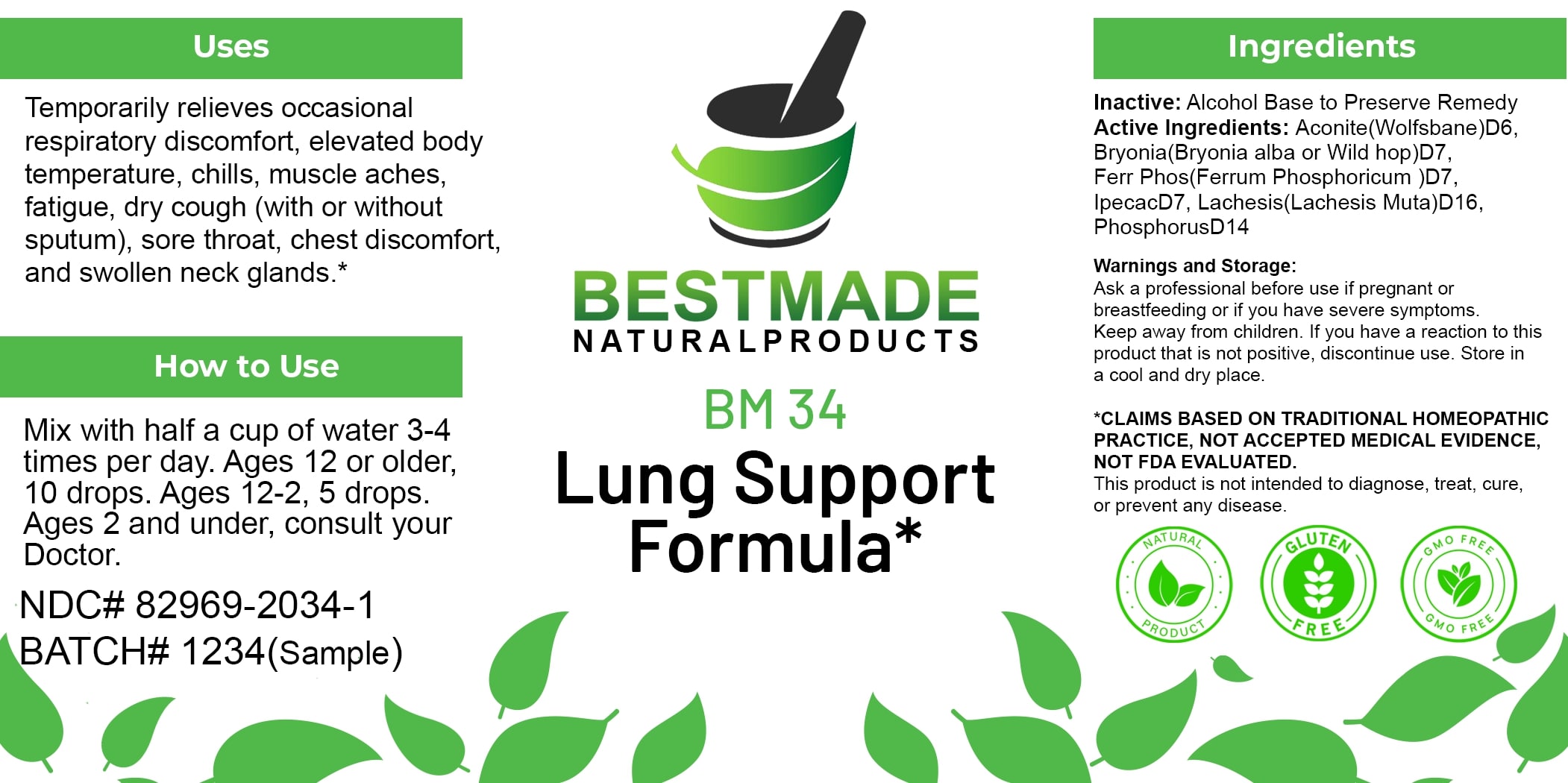 DRUG LABEL: Bestmade Natural Products BM34
NDC: 82969-2034 | Form: LIQUID
Manufacturer: Bestmade Natural Products
Category: homeopathic | Type: HUMAN OTC DRUG LABEL
Date: 20250123

ACTIVE INGREDIENTS: IPECAC 30 [hp_C]/30 [hp_C]; ACONITUM NAPELLUS 30 [hp_C]/30 [hp_C]; BRYONIA ALBA ROOT 30 [hp_C]/30 [hp_C]; FERRIC PYROPHOSPHATE 30 [hp_C]/30 [hp_C]; LACHESIS MUTA VENOM 30 [hp_C]/30 [hp_C]; PHOSPHORUS 30 [hp_C]/30 [hp_C]; ATROPA BELLADONNA 30 [hp_C]/30 [hp_C]
INACTIVE INGREDIENTS: ALCOHOL 30 [hp_C]/30 [hp_C]

BM34

DOSAGE AND ADMINISTRATION

How to Use

Mix with half a cup of water 3-4 times per day. Ages 12 or older, 10 drops. Ages 12-2, 5 drops. Ages 2 and under, consult your Doctor.

Uses

Temporarily relieves occasional respiratory discomfort, elevated body temperature, chills, muscle aches, fatigue, dry cough (with or without sputum), sore throat, chest discomfort, and swollen neck glands.*

*CLAIMS BASED ON TRADITIONAL HOMEOPATHIC PRACTICE, NOT ACCEPTED MEDICAL EVIDENCE, NOT FDA EVALUATED.

This product is not intended to diagnose, treat, cure, or prevent any disease.

Uses

Temporarily relieves occasional respiratory discomfort, elevated body temperature, chills, muscle aches, fatigue, dry cough (with or without sputum), sore throat, chest discomfort, and swollen neck glands.*

*CLAIMS BASED ON TRADITIONAL HOMEOPATHIC PRACTICE, NOT ACCEPTED MEDICAL EVIDENCE, NOT FDA EVALUATED.

This product is not intended to diagnose, treat, cure, or prevent any disease.

ACTIVE INGREDIENT

Active Ingredients: Aconite (Wolfsbane) D6, Bryonia (Bryonia alba or Wild hop) D7, Ferr Phos (Ferrum Phosphoricum) D7, Ipecac D7, Lachesis (Lachesis Muta) D16, Phosphorus D14

INACTIVE INGREDIENT

Ingredients

Inactive: Alcohol Base to Preserve Remedy

KEEP OUT OF REACH OF CHILDREN

Warnings and Storage:

Ask a professional before use if pregnant or breastfeeding or if you have severe symptoms. Keep away from children. If you have a reaction to this product that is not positive, discontinue use. Store in a cool and dry place.

Warnings and Storage:

Ask a professional before use if pregnant or breastfeeding or if you have severe symptoms. Keep away from children. If you have a reaction to this product that is not positive, discontinue use. Store in a cool and dry place.

*CLAIMS BASED ON TRADITIONAL HOMEOPATHIC PRACTICE, NOT ACCEPTED MEDICAL EVIDENCE, NOT FDA EVALUATED.

This product is not intended to diagnose, treat, cure, or prevent any disease.

Entire package label